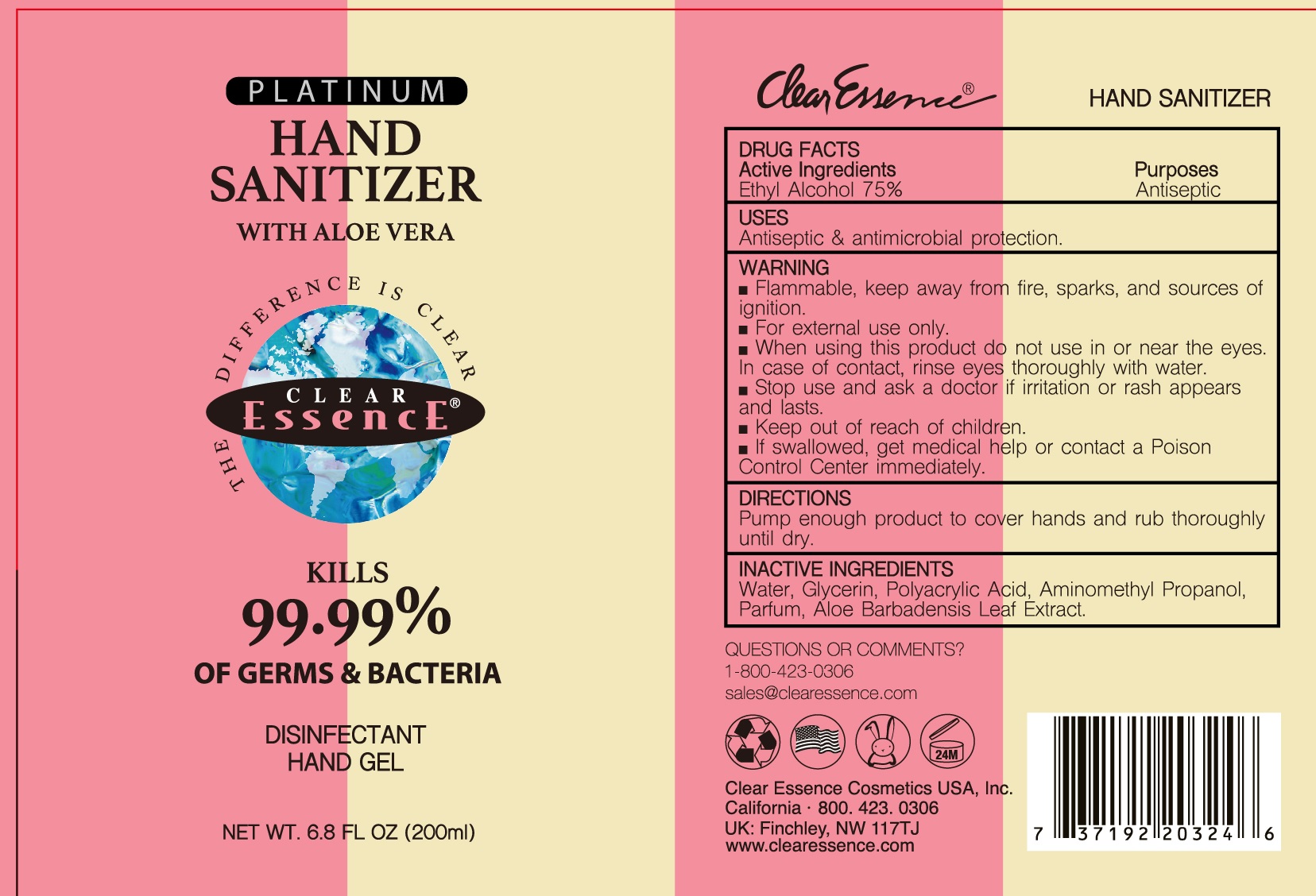 DRUG LABEL: Platinum Hand Sanitizer with Aloe Vera
NDC: 75262-002 | Form: GEL
Manufacturer: ZheJiang Eshine Cosmetic Co Ltd
Category: otc | Type: HUMAN OTC DRUG LABEL
Date: 20250112

ACTIVE INGREDIENTS: ALCOHOL 75 mL/100 mL
INACTIVE INGREDIENTS: WATER; AMINOMETHYLPROPANOL; ALOE VERA LEAF; GLYCERIN

HAND SANITIZER

Active ingredient

Ethyl Alcohol 70%

Purpose

Antiseptic

Use

Antiseptic and antimicrobial protection

Warnings

For external use only.

Flammable.Keep away from fire, sparks, and sources of ignition.

When using this product

do not use in or near the eyes. In case of contact, rinse eyes thoroughly with water.

Stop use and ask a doctor if

irritation or rash appears and lasts.

Keep out of reach of children.

If swallowed, get medical help or contact a Poison Control Center right away.

Directions

Pump enough product to cover hands and rub thoroughly until dry.

Inactive ingredients

Water, Glycerin, Polyacrylic Acid, Aminomethuyl Propanol, Parfum, Aloe Barbadensis Leaf Extract

Questions or comments? 1-800-423-0306